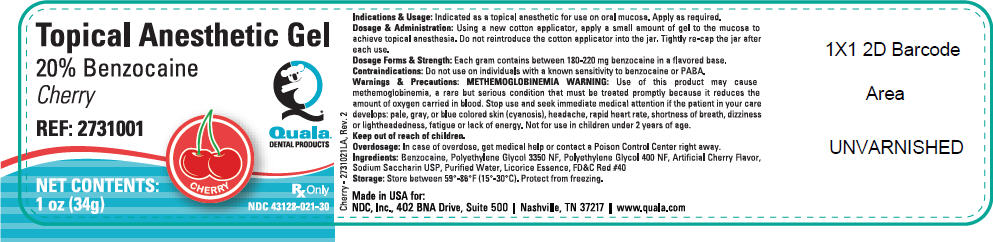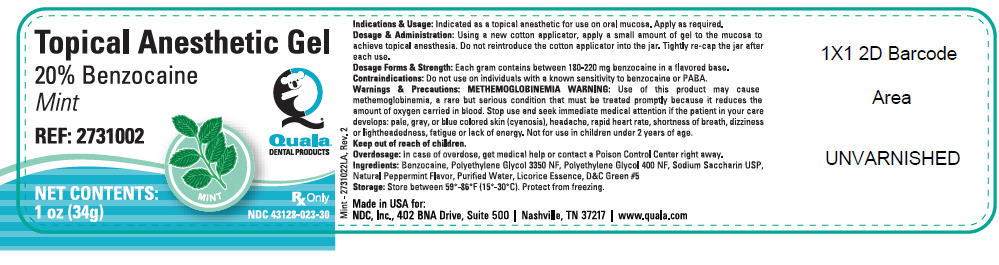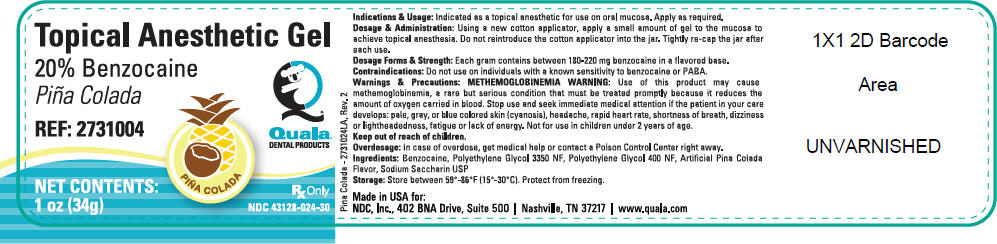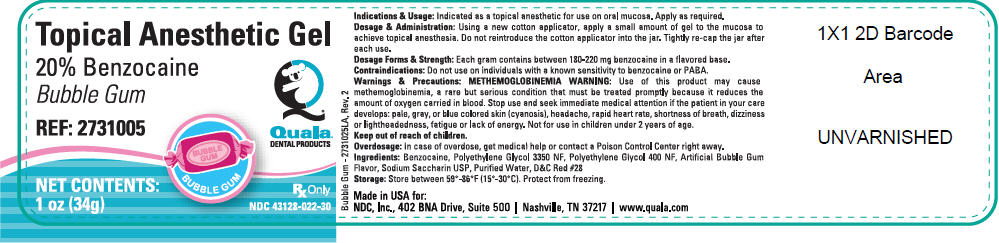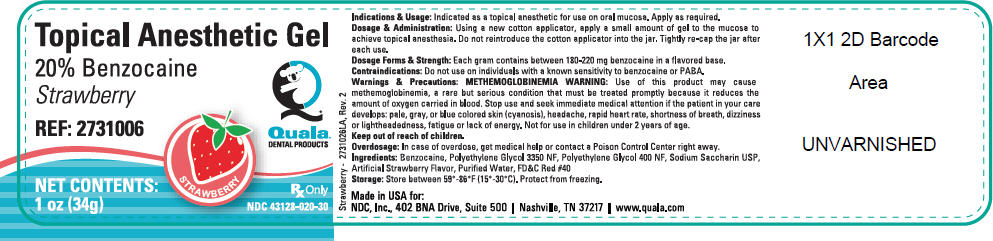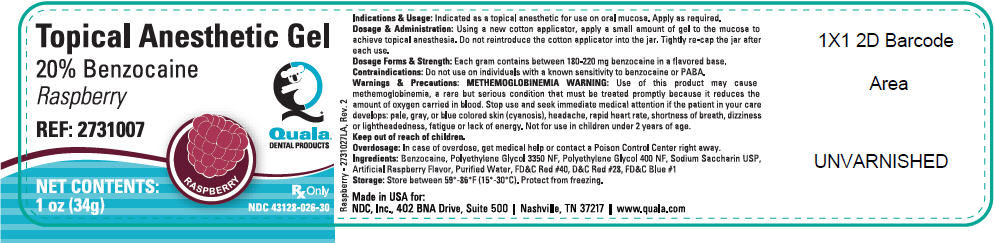 DRUG LABEL: Topical Anesthetic
NDC: 43128-021 | Form: GEL
Manufacturer: NDC, Inc.
Category: prescription | Type: HUMAN PRESCRIPTION DRUG LABEL
Date: 20180904

ACTIVE INGREDIENTS: Benzocaine 220 mg/1 g
INACTIVE INGREDIENTS: Polyethylene Glycol 3350; Polyethylene Glycol 400; Saccharin Sodium; Water; FD&C RED NO. 40

Topical Anesthetic Gel -
20% Benzocaine

Gel – 1oz/34g
2731001 Cherry
2731002 Mint
2731004 Pina Colada
2731005 Bubble Gum
2731006 Strawberry
2731007 Raspberry

For dental use only

Rx only

1. INDICATIONS AND USAGE

Indicated as a topical anesthetic for use on oral mucosa prior to local anesthetic injections, scaling and prophylaxis. Also useful to relieve discomfort associated with taking impressions and intra- oral radiographs.

2. DOSAGE AND ADMINISTRATION

❖ Using a new cotton applicator, apply a small amount of gel to the mucosa to achieve topical anesthesia. Do not reintroduce the cotton applicator into the bottle.
❖ Tightly re-cap the jar after each use.

3. DOSAGE FORMS AND STRENGTH

Each gram of 20% Benzocaine Gel contains between 180-220 mg benzocaine in a flavored base.

4. CONTRAINDICATIONS

Should not be used with individuals with a known sensitivity to benzocaine or PABA.

5. WARNINGS AND PRECAUTIONS

METHEMOGLOBINEMIA WARNING

Use of this product may cause methemoglobinemia, a rare but serious condition that must be treated promptly because it reduces the amount of oxygen carried in blood. Stop use and seek immediate medical attention if the patient in your care develops:

- pale, gray or blue colored skin (cyanosis)
- headache
- rapid heart rate
- shortness of breath
- dizziness or lightheadedness
- fatigue or lack of energy

❖ Not for use in children under 2 years of age
❖ Keep out of reach of children
❖ For professional dental use only
❖ Take care not to contaminate the bottle by reintroducing a used cotton applicator into the bottle

6. OVERDOSAGE

In case of overdose, get medical help or contact a Poison Control Center right away.

7. DESCRIPTION

Flavored 20% benzocaine gel for topical mucosa anesthesia

8. HOW SUPPLIED/STORAGE AND HANDLING

20% benzocaine gel is supplied in multiple use containers

STORAGE AND HANDLING

Store between 59°-86°F (15°-30°C). Protect from freezing.

For more information call NDC at 1-800-929-4232
Manufactured for NDC Nashville, TN 37217
Made in the USA
2731001DF, R1-120116

PRINCIPAL DISPLAY PANEL - 34g Jar Label - Cherry

Topical Anesthetic Gel
20% Benzocaine
Cherry

REF: 2731001

CHERRY

Quala®
DENTAL PRODUCTS

NET CONTENTS:
1 oz (34g)

Rx Only
NDC 43128-021-30

PRINCIPAL DISPLAY PANEL - 34g Jar Label - Mint

Topical Anesthetic Gel
20% Benzocaine
Mint

REF: 2731002

MINT

Quala®
DENTAL PRODUCTS

NET CONTENTS:
1 oz (34g)

Rx Only
NDC 43128-023-30

PRINCIPAL DISPLAY PANEL - 34g Jar Label - Piña Colada

Topical Anesthetic Gel
20% Benzocaine
Piña Colada

REF: 2731004

PIÑA COLADA

Quala®
DENTAL PRODUCTS

NET CONTENTS:
1 oz (34g)

Rx Only
NDC 43128-024-30

PRINCIPAL DISPLAY PANEL - 34g Jar Label - Bubble Gum

Topical Anesthetic Gel
20% Benzocaine
Bubble Gum

REF: 2731005

BUBBLE GUM

Quala®
DENTAL PRODUCTS

NET CONTENTS:
1 oz (34g)

Rx Only
NDC 43128-022-30

PRINCIPAL DISPLAY PANEL - 34g Jar Label - Strawberry

Topical Anesthetic Gel
20% Benzocaine
Strawberry

REF: 2731006

STRAWBERRY

Quala®
DENTAL PRODUCTS

NET CONTENTS:
1 oz (34g)

Rx Only
NDC 43128-020-30

PRINCIPAL DISPLAY PANEL - 34g Jar Label - Raspberry

Topical Anesthetic Gel
20% Benzocaine
Raspberry

REF: 2731007

RASPBERRY

Quala®
DENTAL PRODUCTS

NET CONTENTS:
1 oz (34g)

Rx Only
NDC 43128-026-30